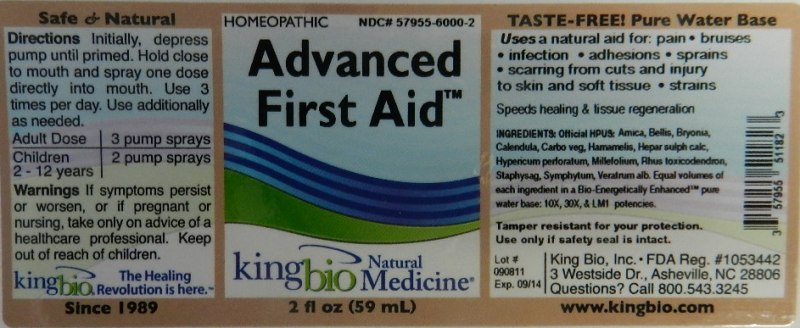 DRUG LABEL: Advanced First Aid
NDC: 57955-6000 | Form: LIQUID
Manufacturer: King Bio Inc.
Category: homeopathic | Type: HUMAN OTC DRUG LABEL
Date: 20111115

ACTIVE INGREDIENTS: ARNICA MONTANA 10 [hp_X]/59 mL; BELLIS PERENNIS 10 [hp_X]/59 mL; BRYONIA ALBA ROOT 10 [hp_X]/59 mL; CALENDULA OFFICINALIS FLOWERING TOP 10 [hp_X]/59 mL; ACTIVATED CHARCOAL 10 [hp_X]/59 mL; HAMAMELIS VIRGINIANA ROOT BARK/STEM BARK 10 [hp_X]/59 mL; CALCIUM SULFIDE 10 [hp_X]/59 mL; HYPERICUM PERFORATUM 10 [hp_X]/59 mL; ACHILLEA MILLEFOLIUM 10 [hp_X]/59 mL; TOXICODENDRON PUBESCENS LEAF 10 [hp_X]/59 mL; DELPHINIUM STAPHISAGRIA SEED 10 [hp_X]/59 mL; COMFREY ROOT 10 [hp_X]/59 mL; VERATRUM ALBUM ROOT 10 [hp_X]/59 mL
INACTIVE INGREDIENTS: WATER

Advanced First Aid

Active Ingredients

Official HPUS: Arnica Montana, Bellis Perennis, Bryonia, Calendula Officinalis, Carbo Vegetabilis, Hamamelis Virginiana, Hepar Sulphuris Calcareum, Hypericum Perforatum, Millefolium, Rhus Toxicodendron, Staphysagria, Symphytum Officinale, and Veratrum Album.

Reference image first aid.jpg

Inactive Ingredient

Equal volumes of each ingredient in a Bio-Energetically Enhanced pure water base. 10X, 30X, and LM1 potencies.

Reference image first aid.jpg

Dosage and Administration

Directions Initially, depress pump until primed. Hold close to mouth and spray one dose directly into mouth. Use 3 times per day. Use additionally as needed.

Adult Dose: 3 pump sprays

Children 2-12 years: 2 pump sprays

Reference image first aid.jpg

Purpose

Uses a natural aid for: pain, bruises, infection, adhesions, sprains, scarring from cuts and injury to skin and soft tissue, and strains.

Speeds healing and tissue regeneration.

Reference image first aid.jpg

Warnings

If symptoms persist or worsen, or if pregnant or nursing, take only on advice of a healthcare professional. Keep out of reach of children.

Tamper resistant for your protection. Use only if safety seal is intact.

Reference image first aid.jpg

Keep out of reach of children.

Reference image first aid.jpg

Indications and Usage

Uses a natural aid for:

- pain
- bruises
- infection
- adhesions
- sprains
- scarring from cuts and injury to skin and soft tissue
- strains

Speeds healing and tissue regeneration.
Reference image first aid.jpg

PACKAGE LABEL

King Bio Inc.
3 Westside Dr.
Asheville, NC 28806
Questions? Call 800.543.3245
www.kingbio.com

Reference image first aid.jpg